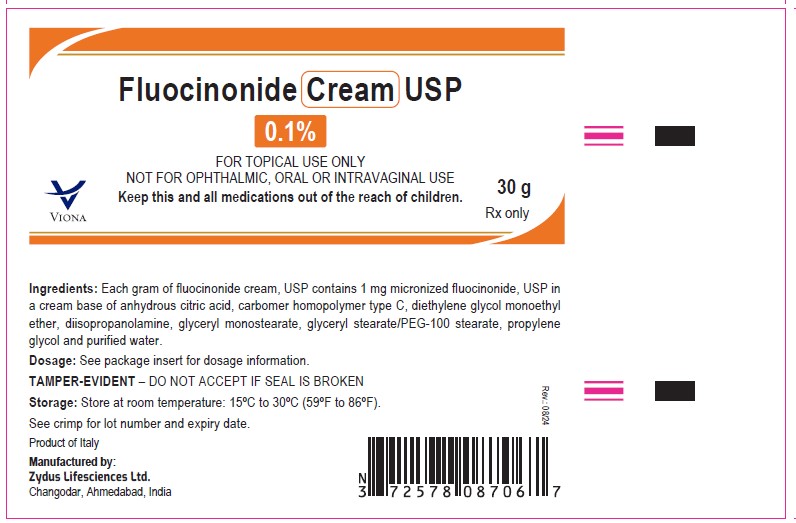 DRUG LABEL: FLUOCINONIDE
NDC: 70771-1393 | Form: CREAM
Manufacturer: Zydus Lifesciences Limited
Category: prescription | Type: HUMAN PRESCRIPTION DRUG LABEL
Date: 20240816

ACTIVE INGREDIENTS: FLUOCINONIDE 1 mg/1 g
INACTIVE INGREDIENTS: ANHYDROUS CITRIC ACID; CARBOMER HOMOPOLYMER TYPE C; DIETHYLENE GLYCOL MONOETHYL ETHER; DIISOPROPANOLAMINE; GLYCERYL MONOSTEARATE; PEG-100 STEARATE; PROPYLENE GLYCOL; WATER

FLUOCINONIDE CREAM

PACKAGE LABEL.PRINCIPAL DISPLAY PANEL

NDC 70771-1393-2

Fluocinonide Cream USP, 0.1%

Rx only

30 g